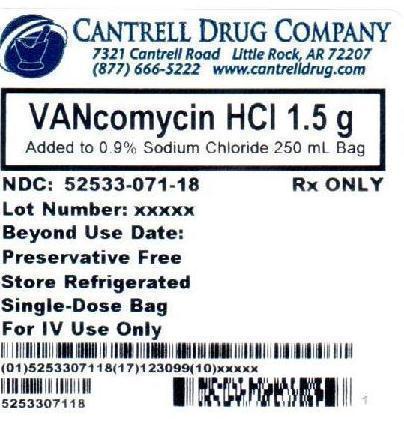 DRUG LABEL: Vancomycin HCl
NDC: 52533-071 | Form: INJECTION, SOLUTION
Manufacturer: Cantrell Drug Company
Category: prescription | Type: HUMAN PRESCRIPTION DRUG LABEL
Date: 20121203

ACTIVE INGREDIENTS: VANCOMYCIN HYDROCHLORIDE 6 mg/1 mL
INACTIVE INGREDIENTS: Sodium Chloride 9 mg/1 mL; Water

Vancomycin HCl 1.5 g Added to 0.9% Sodium Chloride 250 mL Bag